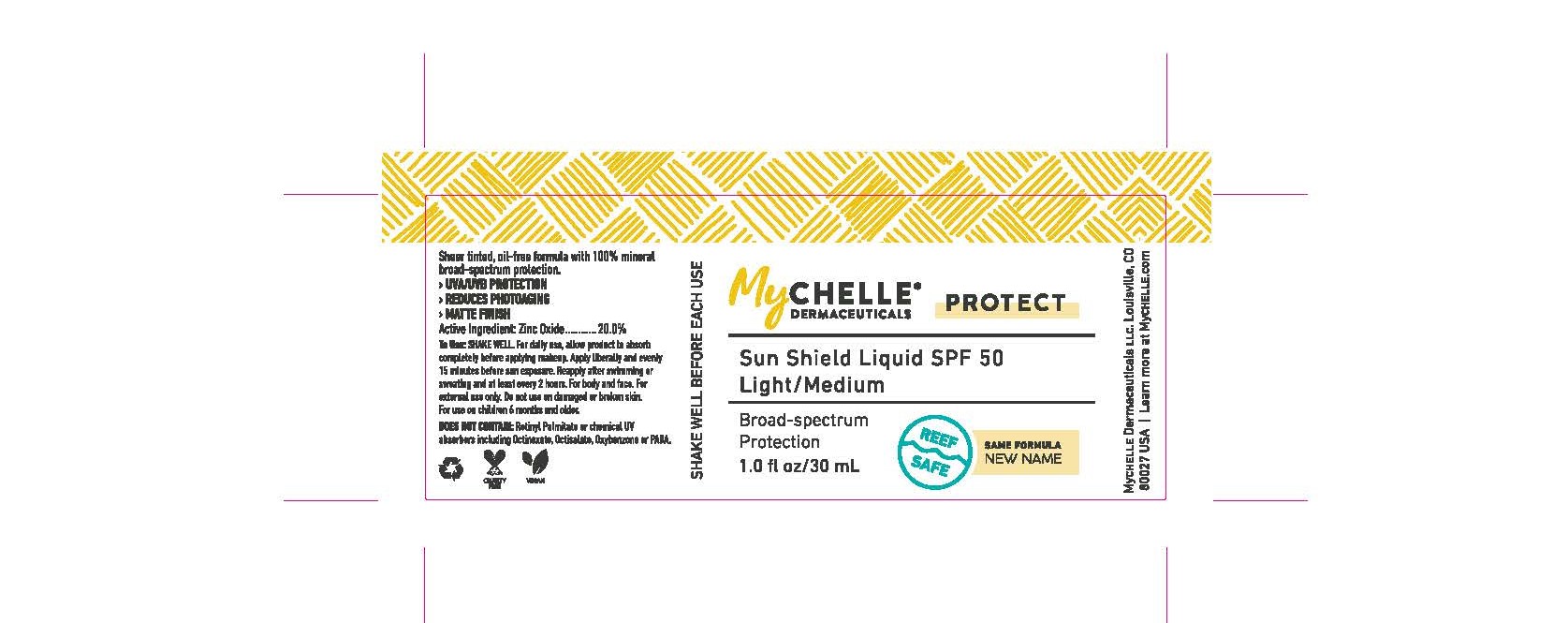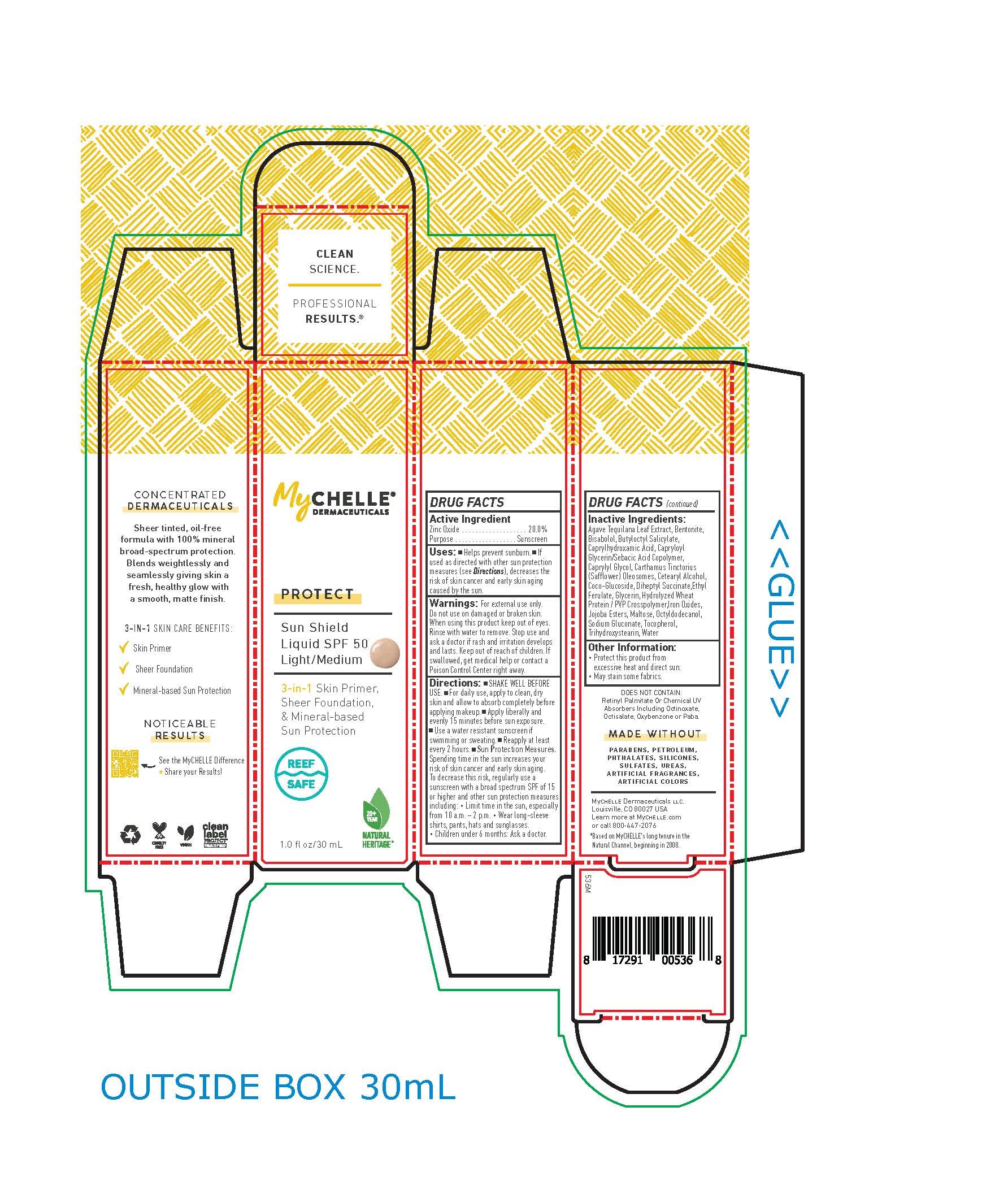 DRUG LABEL: MyChelle Sun Shield Liquid SPF 50 Light/Medium
NDC: 76150-331 | Form: LIQUID
Manufacturer: Bell International Laboratories, Inc
Category: otc | Type: HUMAN OTC DRUG LABEL
Date: 20220120

ACTIVE INGREDIENTS: ZINC OXIDE 20 g/100 mL
INACTIVE INGREDIENTS: LEVOMENOL; TRIHYDROXYSTEARIN; SODIUM GLUCONATE; FERRIC OXIDE RED; OCTYLDODECANOL; FERRIC OXIDE YELLOW; AGAVE TEQUILANA LEAF; BUTYLOCTYL SALICYLATE; CAPRYLHYDROXAMIC ACID; CAPRYLYL GLYCOL; CARTHAMUS TINCTORIUS SEED OLEOSOMES; CETOSTEARYL ALCOHOL; COCO GLUCOSIDE; DIHEPTYL SUCCINATE; ETHYL FERULATE; GLYCERIN; HYDROLYZED WHEAT PROTEIN (ENZYMATIC, 3000 MW); HYDROGENATED JOJOBA OIL, RANDOMIZED; MALTOSE, UNSPECIFIED FORM; BENTONITE; CAPRYLOYL GLYCERIN/SEBACIC ACID COPOLYMER (2000 MPA.S); TOCOPHEROL; FERROSOFERRIC OXIDE

MyChelle Sun Shield Liquid SPF 50 Light/Medium

ACTIVE INGREDIENT

Zinc Oxide 20.0%

PURPOSE

Sunscreen

Uses

Helps prevent sunburn.

If used as directed with other sun protection measures (see DIRECTIONS), decreases the risk of skin cancer and early skin aging caused by the sun.

Warnings

For external use only.

Do not use on damaged or broken skin.

When using this product keep out of eyes.

Rinse with water to remove. Stop use and ask a doctor if rash and irritation develops and lasts.

Keep out of reach of children. If swallowed, get medical help or contact a Poison Control Center right away.

Directions

SHAKE WELL BEFORE USE.
For daily use, apply to clean, dry skin and allow to absorb completely before applying makeup.
Apply liberally and evenly 15 minutes before sun exposure.
Use a water resistant sunscreen if swimming or sweating.
Reapply at least every 2 hours.
Sun Protection Measures. Spending time in the sun increases your risk of skin cancer and early skin aging. To decrease this risk, regularly use a sunscreen with a broad spectrum SPF of 15 or higher and other sun protection measures including:

Limit time in the sun, especially from 10 a.m. – 2 p.m.
Wear long-sleeve shirts, pants, hats and sunglasses.
Children under 6 months: Ask a doctor.

Inactive Ingredients

Agave Tequilana Leaf Extract, Bentonite, Bisabolol, Butyloctyl Salicylate, Caprylhydroxamic Acid, Capryloyl Glycerin/Sebacic Acid Copolymer, Caprylyl Glycol, Carthamus Tinctorius (Safflower) Oleosomes, Cetearyl Alcohol, Coco-Glucoside, Diheptyl Succinate,Ethyl Ferulate, Glycerin, Hydrolyzed Wheat Protein / PVP Crosspolymer,Iron Oxides, Jojoba Esters, Maltose, Octyldodecanol, Sodium Gluconate, Tocopherol, Trihydroxystearin, Water

Other Information

Protect this product from excessive heat and direct sun.

May stain some fabrics.